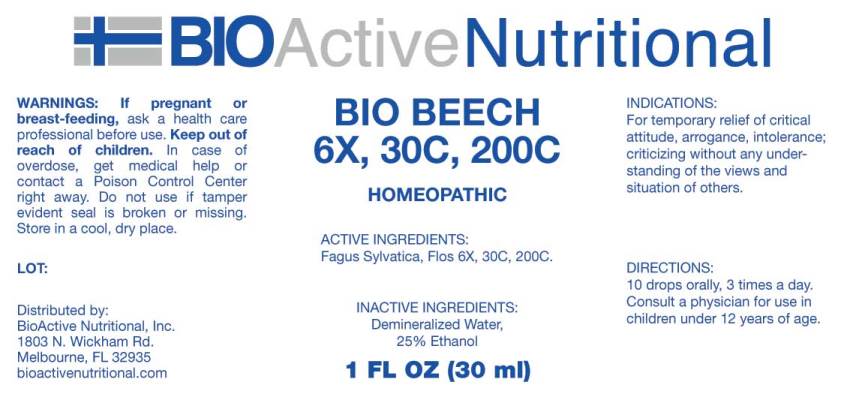 DRUG LABEL: BIO BEECH
NDC: 43857-0189 | Form: LIQUID
Manufacturer: BioActive Nutritional, Inc.
Category: homeopathic | Type: HUMAN OTC DRUG LABEL
Date: 20180410

ACTIVE INGREDIENTS: FAGUS SYLVATICA FLOWERING TOP 6 [hp_X]/1 mL
INACTIVE INGREDIENTS: WATER; ALCOHOL

Drug Facts:

ACTIVE INGREDIENTS:

Fagus Sylvatica, Flos 6X, 30C, 200C.

INDICATIONS:

For temporary relief of critical attitude, arrogance, intolerance; criticizing without any understanding of the views and situation of others.

WARNINGS:

If pregnant or breast-feeding, ask a health care professional before use.

Keep out of reach of children. In case of overdose, get medical help or contact a Poison Control Center right away.

Do not use if tamper evident seal is broken or missing.

STORAGE:

Store in a cool, dry place.

DIRECTIONS:

10 drops orally, 3 times a day. Consult a physician for use in children under 12 years of age.

INACTIVE INGREDIENTS:

Demineralized Water, 25% Ethanol

Keep out of reach of children. In case of overdose, get medical help or contact a Poison Control Center right away.

INDICATIONS:

For temporary relief of critical attitude, arrogance, intolerance; criticizing without any understanding of the views and situation of others.

QUESTIONS:

Distributed by:
BioActive Nutritional, Inc.
1803 N. Wickham Rd.
Melbourne, FL 32935
bioactivenutritional.com

PACKAGE DISPLAY LABEL:

BIOActive Nutritional

BIO BEECH

6X, 30C, 200C

HOMEOPATHIC

1 FL OZ (30 mL)